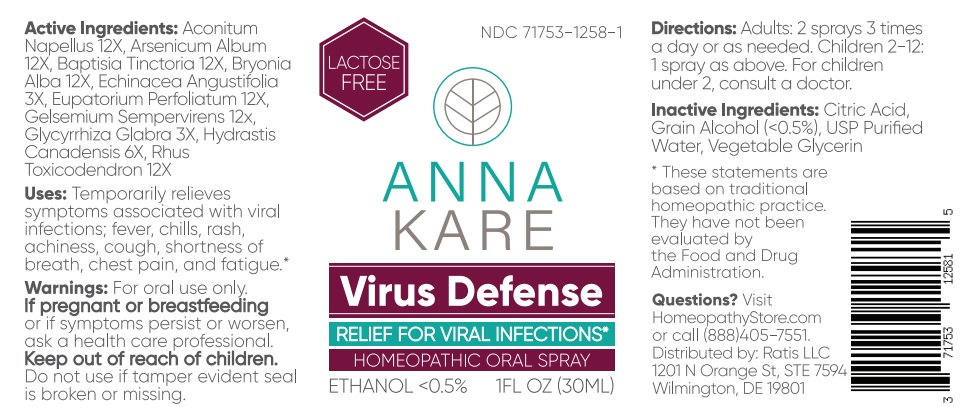 DRUG LABEL: Virus Defense ANNAKARE
NDC: 71753-1258 | Form: SPRAY
Manufacturer: Ratis, LLC
Category: homeopathic | Type: HUMAN OTC DRUG LABEL
Date: 20251003

ACTIVE INGREDIENTS: ACONITUM NAPELLUS ROOT 12 [hp_X]/30 mL; ARSENIC TRIOXIDE 12 [hp_X]/30 mL; BAPTISIA TINCTORIA ROOT 12 [hp_X]/30 mL; BRYONIA ALBA ROOT 12 [hp_X]/30 mL; ECHINACEA ANGUSTIFOLIA WHOLE 3 [hp_X]/30 mL; EUPATORIUM PERFOLIATUM WHOLE 12 [hp_X]/30 mL; GELSEMIUM SEMPERVIRENS WHOLE 12 [hp_X]/30 mL; GLYCYRRHIZA GLABRA 3 [hp_X]/30 mL; HYDRASTIS CANADENSIS WHOLE 6 [hp_X]/30 mL; TOXICODENDRON PUBESCENS LEAF 12 [hp_X]/30 mL
INACTIVE INGREDIENTS: WATER; GLYCERIN; CITRIC ACID MONOHYDRATE; ALCOHOL

Drug Facts:

Active Ingredients

Aconitum napellus 12X, Arsenicum album 12X, Baptisia Tinctoria 12X, Bryonia alba 12X, Echinacea angustifolia 3X, Eupatorium perfoliatum 12X, Gelsemium sempervirens 12X, Glycyrrhiza glabra 3X, Hydrastis canadensis 6X, Rhus Toxicodendron 12X

Uses

Temporarily relieves symptoms associated with viral infections; fever, chills, rash, achiness, cough, shortness of breath, chest pain, and fatigue.**

**These statements are based upon traditional homeopathic practice. They have not been reviewed by the Food and Drug Administration.

Warning

For oral use only.

If pregnant or breast-feeding,or if symptoms persist or worsen, ask a health care professional.

Keep out of reach of children.

Do not use if tamper evident seal is broken or missing.

Direction

Adults: 2 sprays 3 times a day or as needed.

Children 2-12: 1 spray as above. For children under 2, consult a doctor.

Inactive Ingredients

Citric Acid, USP purified Water, Grain alcohol (<0.5%), vegetable Glycerin

Questions?

Visit HomeopathyStore.com

or call (888) 405-7551.

Distributed by: Ratis, LLC,

1201 N. Orange St, STE 7594,

Wilmington, DE 19801